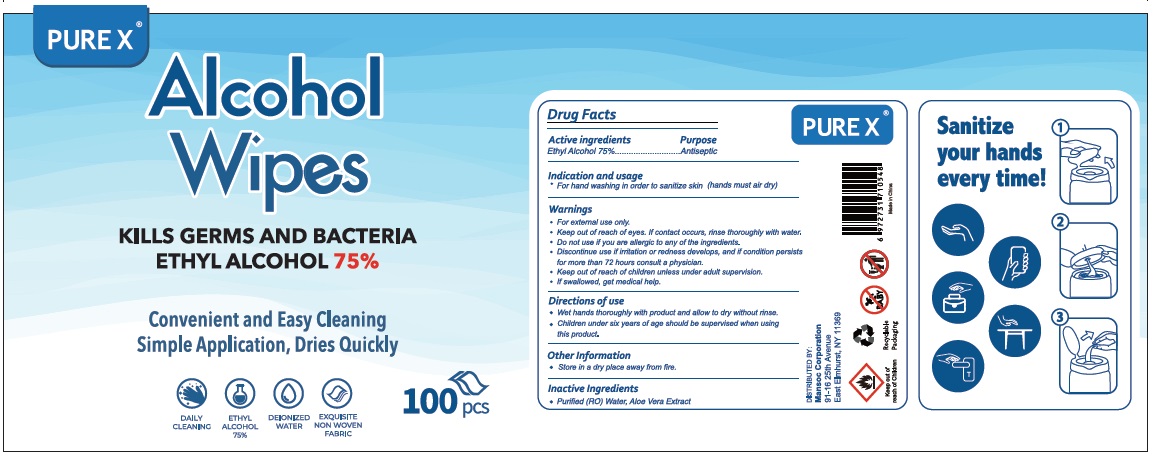 DRUG LABEL: PURE X Alcohol Wipes
NDC: 80671-002 | Form: CLOTH
Manufacturer: QUANZHOU AIWINA HYGIENE PRODUCTS CO.,LTD
Category: otc | Type: HUMAN OTC DRUG LABEL
Date: 20210212

ACTIVE INGREDIENTS: ALCOHOL 75 mL/100 mL
INACTIVE INGREDIENTS: WATER; ALOE VERA LEAF

PURE X® Alcohol Wipes

Active ingredients

Ethyl Alcohol 75%

Purpose

Antiseptic

Indication and usage

- For hand washing in order to sanitize skin (hands must air dry)

Warnings

- For external use only.
- Keep out of reach of eyes. If contact occurs, rinse thoroughly with water.
- Do not use if you are allergic to any of the ingredients.
- Discontinue use if irritation or redness develops, and if condition persists for more than 72 hours consult a physician.

- Keep out of reach of children unless under adult supervision.
- If swallowed, get medical help.

Directions of use

- Wet hands thoroughly with product and allow to dry without rinse.
- Children under six years of age should be supervised when using this product.

Other Information

- Store in a dry place away from fire.

Inactive Ingredients

- Purified (RO) Water, Aloe Vera Extract

KILLS GERMS AND BACTERIA

ETHYL ALCOHOL 75%

Convenient and Easy Cleaning

Simple Application, Dries Quickly

DAILY CLEANING

DEIONIZED WATER

EXQUISITE NON WOVEN FABRIC

DISTRIBUTED BY:

Mansoc Corporation

91-16 25th Avenue

East Elmhurst, NY 11369

Keep out of reach of Children

Made in China

Sanitize your hands every time!